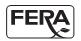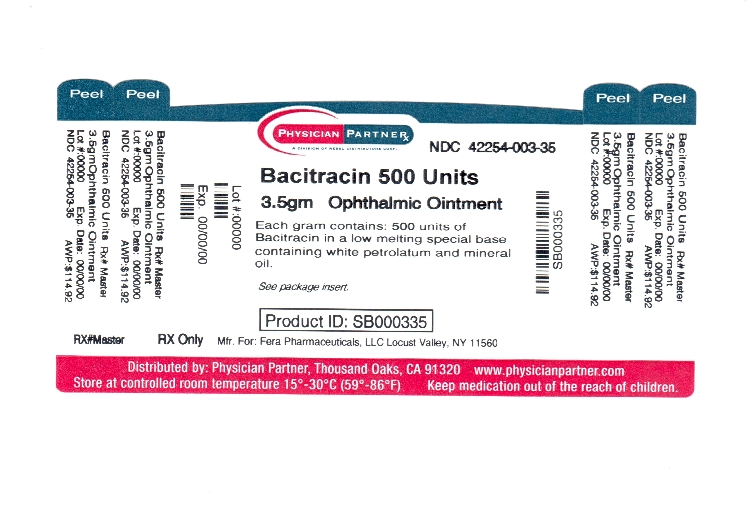 DRUG LABEL: BACITRACIN
NDC: 42254-003 | Form: OINTMENT
Manufacturer: Rebel Distributors Corp
Category: prescription | Type: HUMAN PRESCRIPTION DRUG LABEL
Date: 20111102

ACTIVE INGREDIENTS: BACITRACIN 500 [iU]/1 g
INACTIVE INGREDIENTS: MINERAL OIL; PETROLATUM

BACITRACIN
OPHTHALMIC
OINTMENT USP
STERILE

Rx Only

DESCRIPTION:

Each gram of ointment contains 500 units of Bacitracin in a low melting special base containing White Petrolatum and Mineral Oil.

ACTION:

The antibiotic, Bacitracin, exerts a profound action against many gram-positive pathogens, including the common Streptococci and Staphylococci. It is also destructive for certain gram-negative organisms. It is ineffective against fungi.

INDICATIONS:

For the treatment of superficial ocular infections involving the conjunctiva and/or cornea caused by Bacitracin susceptible organisms.

CONTRAINDICATIONS:

This product should not be used in patients with a history of hypersensitivity to Bacitracin.

PRECAUTIONS:

Bacitracin ophthalmic ointment should not be used in deep-seated ocular infections or in those that are likely to become systemic. The prolonged use of antibiotic containing preparations may result in overgrowth of nonsusceptible organisms particularly fungi. If new infections develop during treatment appropriate antibiotic or chemotherapy should be instituted.

ADVERSE REACTIONS:

Bacitracin has such a low incidence of allergenicity that for all practical purposes side reactions are practically non-existent. However, if such reaction should occur, therapy should be discontinued.

DOSAGE AND ADMINISTRATION:

The ointment should be applied directly into the conjunctival sac 1 to 3 times daily. In blepharitis all scales and crusts should be carefully removed and the ointment then spread uniformly over the lid margins. Patients should be instructed to take appropriate measures to avoid gross contamination of the ointment when applying the ointment directly to the infected eye.

HOW SUPPLIED:

3.5 g (1/8 Oz) sterile tamper proof tubes, NDC 42254-003-35.

Manufactured for:

Fera Pharmaceuticals, LLC
Locust Valley, NY 11560

FPBC00N Rev. 08/09

Repackaged by:

Rebel Distributors Corp

Thousand Oaks, CA 91320